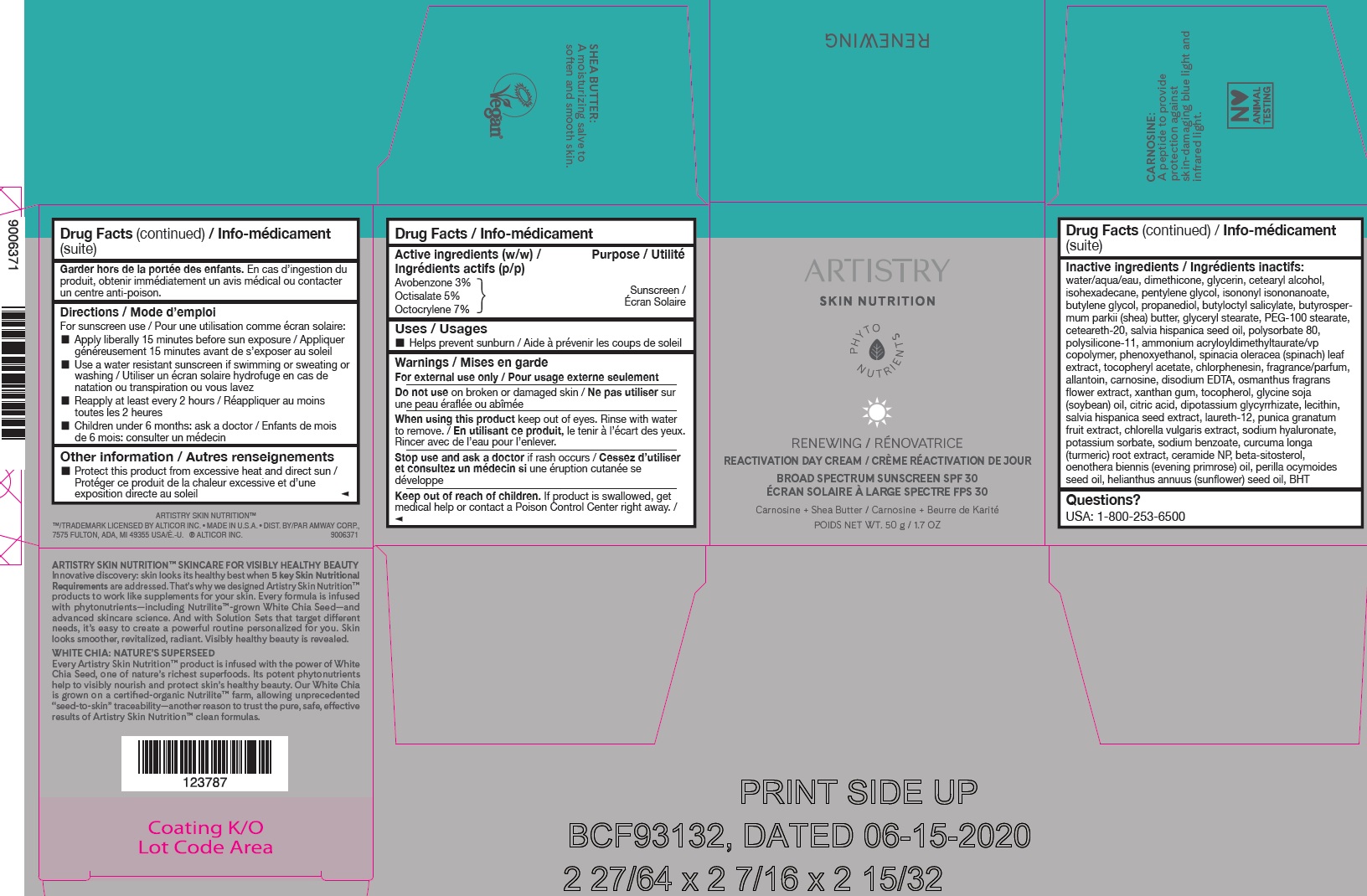 DRUG LABEL: Artistry Skin Nutrition RENEWING Reactivation Day Cream SPF 30
NDC: 10056-050 | Form: CREAM
Manufacturer: Access Business Group LLC
Category: otc | Type: HUMAN OTC DRUG LABEL
Date: 20231021

ACTIVE INGREDIENTS: AVOBENZONE 30 mg/1 g; OCTISALATE 50 mg/1 g; OCTOCRYLENE 70 mg/1 g
INACTIVE INGREDIENTS: .ALPHA.-TOCOPHEROL ACETATE; CHLORPHENESIN; ALLANTOIN; CARNOSINE; EDETATE DISODIUM ANHYDROUS; OSMANTHUS FRAGRANS FLOWER; XANTHAN GUM; TOCOPHEROL; SOYBEAN OIL; CITRIC ACID MONOHYDRATE; GLYCYRRHIZINATE DIPOTASSIUM; CHIA SEED; LAURETH-12; POMEGRANATE; CHLORELLA VULGARIS; HYALURONATE SODIUM; POTASSIUM SORBATE; SODIUM BENZOATE; TURMERIC; CERAMIDE NP; .BETA.-SITOSTEROL; EVENING PRIMROSE OIL; PERILLA FRUTESCENS SEED OIL; SUNFLOWER OIL; BUTYLATED HYDROXYTOLUENE; BUTYLENE GLYCOL; PROPANEDIOL; BUTYLOCTYL SALICYLATE; SHEA BUTTER; GLYCERYL MONOSTEARATE; PEG-100 STEARATE; POLYOXYL 20 CETOSTEARYL ETHER; CHIA SEED OIL; POLYSORBATE 80; WATER; DIMETHICONE; GLYCERIN; CETOSTEARYL ALCOHOL; ISOHEXADECANE; PENTYLENE GLYCOL; ISONONYL ISONONANOATE; DIMETHICONE/VINYL DIMETHICONE CROSSPOLYMER (SOFT PARTICLE); AMMONIUM ACRYLOYLDIMETHYLTAURATE/VP COPOLYMER; PHENOXYETHANOL; SPINACH

Artistry Skin Nutrition RENEWING Reactivation Day Cream SPF 30

Active ingredients (w/w)

Avobenzone 3% Octisalate 5% Octocrylene 7%

Purpose

Sunscreen

Uses

- Helps prevent sunburn

Warnings

For external use only

Do not use

on broken or damaged skin

When using this product

keep out of eyes. Rinse with water to remove.

Stop use and ask a doctor

if rash occurs

Keep out of reach of children.

If product is swallowed, get medical help or contact a Poison Control Center right away.

Directions

For sunscreen use

- Apply liberally 15 minutes before sun exposure
- Use a water resistant sunscreen if swimming or sweating or washing
- Reapply at least every 2 hours
- Children under 6 months: ask a doctor

Other information

- Protect this product from excessive heat and direct sun

Inactive ingredients

water, dimethicone, glycerin, cetearyl alcohol, isohexadecane, pentylene glycol, isononyl isononanoate, butylene glycol, propanediol, butyloctyl salicylate, butyrospermum parkii (shea) butter, glyceryl stearate, PEG-100 stearate, ceteareth-20, salvia hispanica seed oil, polysorbate 80, polysilicone-11, ammonium acryloyldimethyltaurate/vp copolymer, phenoxyethanol, spinacia oleracea (spinach) leaf extract, tocopheryl acetate, chlorphenesin, fragrance/parfum, allantoin, carnosine, disodium EDTA, osmanthus fragrans flower extract, xanthan gum, tocopherol, glycine soja (soybean) oil, citric acid, dipotassium glycyrrhizate, lecithin, salvia hispanica seed extract, laureth-12, punica granatum fruit extract, chlorella vulgaris extract, sodium hyaluronate, potassium sorbate, sodium benzoate, curcuma longa (turmeric) root extract, ceramide NP, beta-sitosterol, oenothera biennis (evening primrose) oil, perilla ocymoides seed oil, helianthus annuus (sunflower) seed oil, BHT

Questions?

USA: 1-800-253-6500